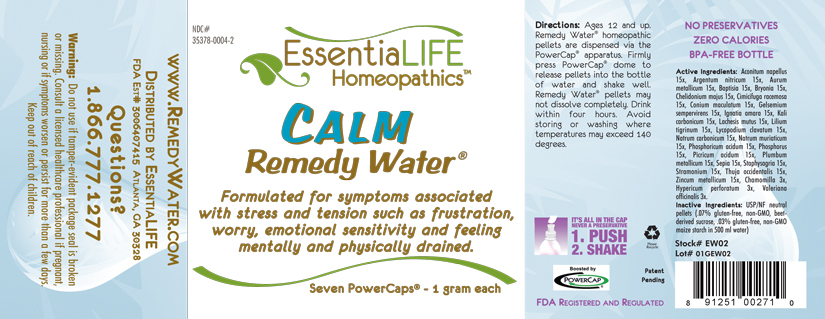 DRUG LABEL: Calm Remedy Water 
NDC: 35378-0004 | Form: PELLET
Manufacturer: Georgetown Health, LLC DBA EssentiaLife
Category: homeopathic | Type: HUMAN OTC DRUG LABEL
Date: 20120610

ACTIVE INGREDIENTS: Aconitum Napellus 15 [hp_X]/1 mg; Silver Nitrate 15 [hp_X]/1 mg; Gold 15 [hp_X]/1 mg; Baptisia Tinctoria Root 15 [hp_X]/1 mg; Bryonia Alba Root 15 [hp_X]/1 mg; Chelidonium Majus 15 [hp_X]/1 mg; Black Cohosh 15 [hp_X]/1 mg; Conium Maculatum Flowering Top 15 [hp_X]/1 mg; Gelsemium Sempervirens Root 15 [hp_X]/1 mg; Strychnos Ignatii Seed 15 [hp_X]/1 mg; Potassium Carbonate 15 [hp_X]/1 mg; Lachesis Muta Venom 15 [hp_X]/1 mg; Lilium Lancifolium Bulb 15 [hp_X]/1 mg; Lycopodium Clavatum Spore 15 [hp_X]/1 mg; Sodium Carbonate 15 [hp_X]/1 mg; Sodium Chloride 15 [hp_X]/1 mg; Phosphoric Acid 15 [hp_X]/1 mg; Phosphorus 15 [hp_X]/1 mg; Trinitrophenol 15 [hp_X]/1 mg; Lead 15 [hp_X]/1 mg; Sepia Officinalis Juice 15 [hp_X]/1 mg; Delphinium Staphisagria Seed 15 [hp_X]/1 mg; Datura Stramonium 15 [hp_X]/1 mg; Thuja Occidentalis Leafy Twig 15 [hp_X]/1 mg; Zinc 15 [hp_X]/1 mg; Matricaria Recutita 3 [hp_X]/1 mg; Hypericum Perforatum 3 [hp_X]/1 mg; Valerian 3 [hp_X]/1 mg
INACTIVE INGREDIENTS: Starch, Corn; Sucrose

Calm Remedy Water®

Active Ingredients

Aconitum napellus | 15x
Argentum nitricum | 15x
Aurum metallicum | 15x
Baptisia | 15x
Bryonia | 15x
Chelidonium majus | 15x
Cimicifuga racemosa | 15x
Conium maculatum | 15x
Gelsemium sempervirens | 15x
Ignatia amara | 15x
Kali carbonicum | 15x
Lachesis mutus | 15x
Lilum tigrinum | 15x
Lycopodium clavatum | 15x
Natrum carbonicum | 15x
Natrum muriaticum | 15x
Phosphoricum acidum | 15x
Phosphorus | 15x
Picricum acidum | 15x
Plumbum metallicum | 15x
Sepia | 15x
Staphysagria | 15x
Stramonium | 15x
Thuja occidentalis | 15x
Zincum metallicum | 15x
Chamomilla | 3x
Hypericum perforatum | 3x
Valeriana officinalis | 3x

Purpose

Formulated for symptoms associated with stress and tension such as worry, frustration, emotional sensitivity and feeling mentally and physically drained.

Uses

Formulated for symptoms associated with stress and tension such as worry, frustration, emotional sensitivity and feeling mentally and physically drained.

Warnings

Do not use if tamper-evident package seal is broken or missing. Consult a licensed healthcare professional if pregnant, nursing or if symptoms worsen or persist for more than a few days. Keep out of reach of children.

Directions

Ages 12 and up. Remedy Water® homepathic pellets are dispersed via the PowerCap® apparatus. Firmly press PowerCap® dome to release pellets into the bottle of water and shake well. Remedy Water® pellets may not dissolve completely. Drink within four hours. Avoid storing or washing where temperatures may exceed 140 degrees.

Inactive Ingredients

USP/NF neutral pellets (.07% gluten-free, non-GMO, beet-derived sucrose, .03% gluten-free, non-GMO maize starch in 500 ml water)

Other Information

Avoid storing in areas where temperatures may exceed 140 degrees.

Questions?

1.866.777.1277
www.RemedyWater.com

PRINCIPAL DISPLAY PANEL

NDC# 35378-0004-2

EssentiaLIFE Homeopathics™

CALM Remedy Water®

Formulated for symptoms associated with stress and tension such as frustration, worry, emotional sensitivity and feeling mentally and physically drained.

Seven PowerCaps® - 1 gram each

Directions: Ages 12 and up. Remedy Water® homepathic pellets are dispersed via the PowerCap® apparatus. Firmly press PowerCap® dome to release pellets into the bottle of water and shake well. Remedy Water® pellets may not dissolve completely. Drink within four hours. Avoid storing or washing where temperatures may exceed 140 degrees.

IT'S ALL IN THE CAP
NEVER A PRESERVATIVE
1. PUSH
2. SHAKE

Please Recyle

Patent Pending

Boosted by PowerCap®

FDA Registered and Regulated

NO PRESERVATIVES
ZERO CALORIES
BPA-FREE BOTTLE

Active Ingredients: Aconitum napellus 15x, Argentum nitricum 15x, Aurum metallicum 15x, Baptisia 15x, Bryonia 15x, Chelidonium majus 15x, Cimicifuga racemosa 15x, Conium maculatum 15x, Gelsemium sempervirens 15x, Ignatia amara 15x, Kali carbonicum 15x, Lachesis mutus 15x, Lilium tigrinum 15x, Lycopodium clavatum 15x, Natrum carbonicum 15x, Natrum muriaticum 15x, Phosphoricum acidum 15x, Phosphorus 15x, Picricum acidum 15x, Plumbum metallicum 15x, Sepia 15x, Staphysagria 15x, Stramonium 15x, Thuja occidentalis 15x, Zincum metallicum 15x, Chamomilla 3x, Hypericum perforatum 3x, Valeriana officinalis 3x.

Inactive ingredients: USP/NF neutral pellets (.07% gluten-free, non-GMO, beet-derived sucrose, .03% gluten-free, non-GMO maize starch in 500 ml water)

Stock# EW02

Lot# 01GEW02

www.RemedyWater.com

Distributed by EssentiaLIFE

FDA Est.# 3006407415 Atlanta, GA 30328

Questions?

1.866.777.1277

Warning: Do not use if tamper-evident package seal is broken or missing. Consult a licensed healthcare professional if pregnant, nursing or if symptoms worsen or persist for more than a few days. Keep out of reach of children.